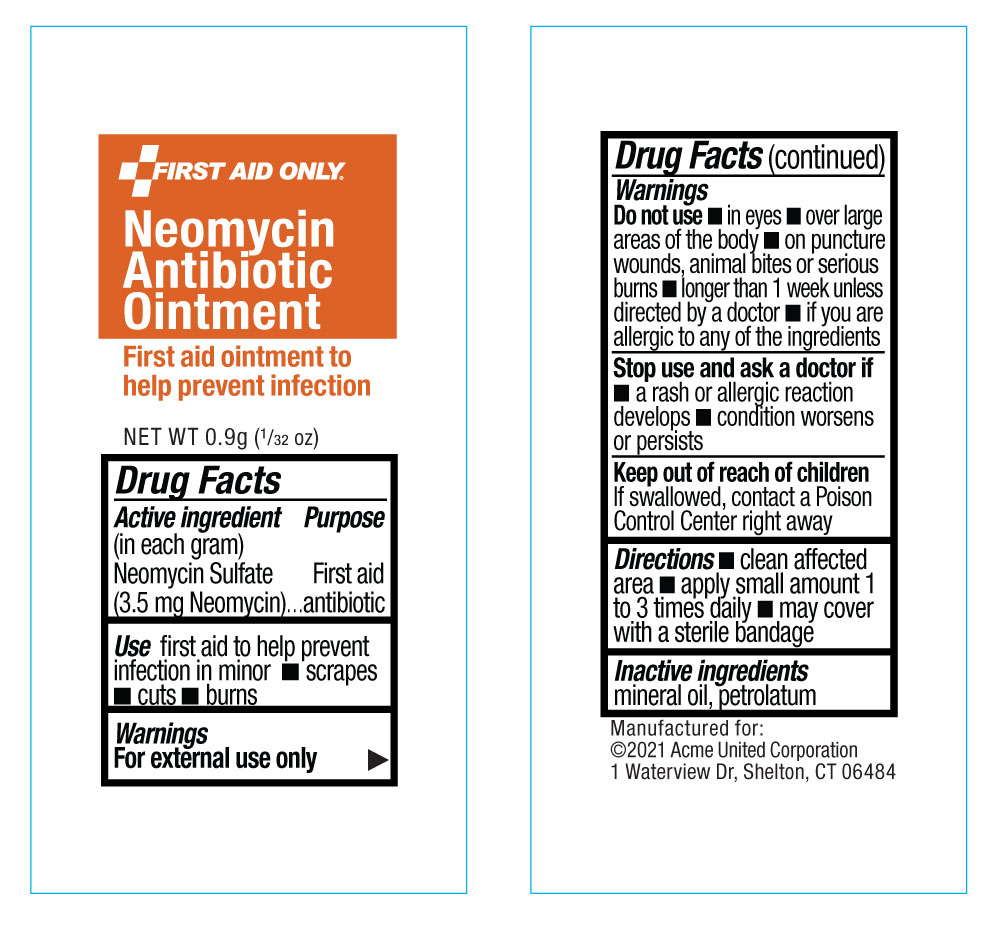 DRUG LABEL: First Aid Only Neomycin Antibiotic
NDC: 0924-5620 | Form: OINTMENT
Manufacturer: Acme United Corporation
Category: otc | Type: HUMAN OTC DRUG LABEL
Date: 20241119

ACTIVE INGREDIENTS: NEOMYCIN SULFATE 3.5 mg/1 g
INACTIVE INGREDIENTS: PETROLATUM

FIRST AID ONLY Neomycin Antibiotic Ointment

Drug Facts

Active Ingredient (in each gram)

Neomycin Sulfate (3.5 mg Neomycin)

Purpose

First Aid Antibiotic

Uses:

First aid to help prevent infection in minor cuts, scrapes, burns.

INDICATIONS AND USAGE

Use firstaid to help prevent infection in minor •scrapes •cuts •burns

Warnings:

For external use only.

Keep out of reach of children.

If swallowed, contact a Poison Control Center right away

Do Not Use:

- in the eyes • over large areas of the body •on puncture wounds, animal bites or serious burns
- longer than 1 week unless directed by a doctor
- if you are allergic to any of the ingredients

Stop use, ask a doctor if

- a rash or allergic reaction develop
- condition persists or gets worse

Directions

- clean affected area
- apply small amount 1 to 3 times daily
- may cover with a sterile bandage

Inactive ingredients:

mineral oil, petrolatum

Manufactured for:

©2021 Acme United Corporation

1 Waterview Dr, Shelton, CT 06484

Pouch Label